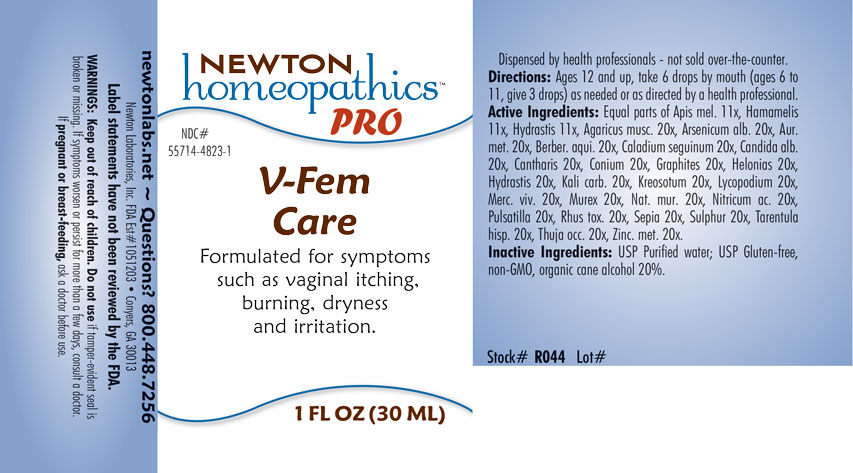 DRUG LABEL: V-Fem Care
NDC: 55714-4823 | Form: LIQUID
Manufacturer: Newton Laboratories, Inc.
Category: homeopathic | Type: HUMAN OTC DRUG LABEL
Date: 20201207

ACTIVE INGREDIENTS: AMANITA MUSCARIA FRUITING BODY 20 [hp_X]/1 mL; ARSENIC TRIOXIDE 20 [hp_X]/1 mL; GOLD 20 [hp_X]/1 mL; BERBERIS AQUIFOLIUM ROOT BARK 20 [hp_X]/1 mL; DIEFFENBACHIA SEGUINE 20 [hp_X]/1 mL; CANDIDA ALBICANS 20 [hp_X]/1 mL; LYTTA VESICATORIA 20 [hp_X]/1 mL; CONIUM MACULATUM FLOWERING TOP 20 [hp_X]/1 mL; GRAPHITE 20 [hp_X]/1 mL; CHAMAELIRIUM LUTEUM ROOT 20 [hp_X]/1 mL; GOLDENSEAL 20 [hp_X]/1 mL; POTASSIUM CARBONATE 20 [hp_X]/1 mL; WOOD CREOSOTE 20 [hp_X]/1 mL; LYCOPODIUM CLAVATUM SPORE 20 [hp_X]/1 mL; MERCURY 20 [hp_X]/1 mL; HEXAPLEX TRUNCULUS HYPOBRANCHIAL GLAND JUICE 20 [hp_X]/1 mL; TOXICODENDRON PUBESCENS LEAF 20 [hp_X]/1 mL; SODIUM CHLORIDE 20 [hp_X]/1 mL; NITRIC ACID 20 [hp_X]/1 mL; ANEMONE PULSATILLA 20 [hp_X]/1 mL; SEPIA OFFICINALIS JUICE 20 [hp_X]/1 mL; SULFUR 20 [hp_X]/1 mL; LYCOSA TARANTULA 20 [hp_X]/1 mL; THUJA OCCIDENTALIS LEAFY TWIG 20 [hp_X]/1 mL; ZINC 20 [hp_X]/1 mL; APIS MELLIFERA 11 [hp_X]/1 mL; HAMAMELIS VIRGINIANA ROOT BARK/STEM BARK 11 [hp_X]/1 mL
INACTIVE INGREDIENTS: WATER; ALCOHOL

V-Fem 4823L

INDICATIONS & USAGE SECTION

Formulated for symptoms such as vaginal itching, burning, dryness and irritation.

DOSAGE & ADMINISTRATION SECTION

Directions: Ages 12 and up, take 6 drops by mouth (ages 6 to 11, give 3 drops) as needed or as directed by a health professional.

OTC - ACTIVE INGREDIENT SECTION

Equal parts of Apis mellifica 11x, Hamamelis virginiana 11x, Hydrastis canadensis 11x, Agaricus muscarius 20x, Arsenicum album 20x, Aurum metallicum 20x, Berberis aquifolium 20x, Caladium seguinum 20x, Candida albicans 20x, Cantharis 20x, Conium maculatum 20x, Graphites 20x, Helonias dioica 20x, Hydrastis canadensis 20x, Kali carbonicum 20x, Kreosotum 20x, Lycopodium clavatum 20x, Mercurius vivus 20x, Murex purpurea 20x, Natrum muriaticum 20x, Nitricum acidum 20x, Pulsatilla 20x, Rhus toxicodendron 20x, Sepia 20x, Sulphur 20x, Tarentula hispana 20x, Thuja occidentalis 20x, Zincum metallicum 20x.

OTC - PURPOSE SECTION

Formulated for symptoms such as vaginal itching, burning, dryness and irritation.

INACTIVE INGREDIENT SECTION

Inactive Ingredients: USP Purified Water; USP Gluten-free, non-GMO, organic cane alcohol 20%.

QUESTIONS SECTION

newtonlabs.net – Questions? 800.448.7256

Newton Laboratories, Inc. FDA Est # 1051203 - Conyers, GA 30013

WARNINGS SECTION

WARNINGS: Keep out of reach of children. Do not use if tamper-evident seal is broken or missing. If symptoms worsen or persist for more than a few days, consult a doctor. If pregnant or breast-feeding, ask a doctor before use.

OTC - PREGNANCY OR BREAST FEEDING SECTION

If pregnant or breast-feeding, ask a doctor before use.

OTC - KEEP OUT OF REACH OF CHILDREN SECTION

Keep out of reach of children.